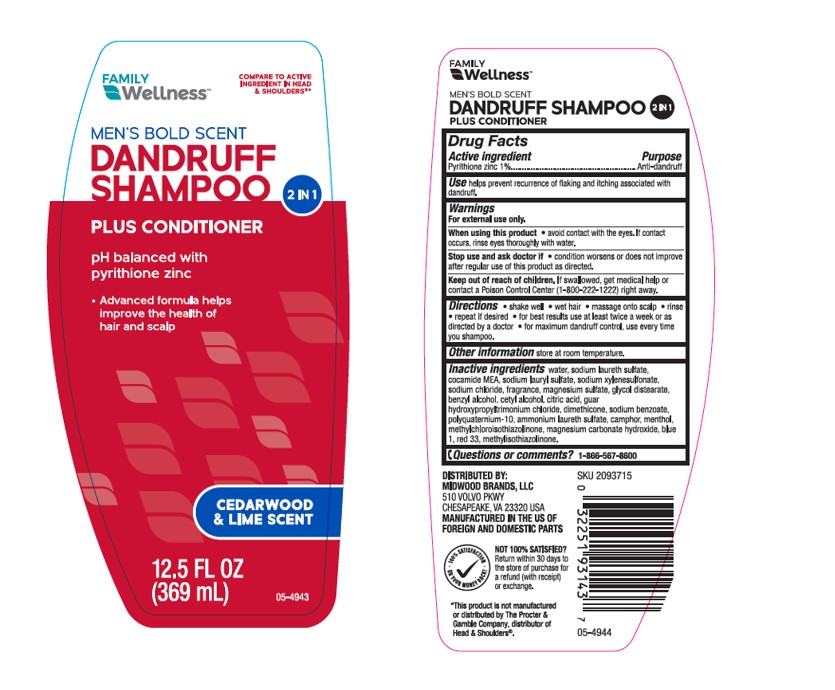 DRUG LABEL: Equate Mens Bold Scent 2 in 1 Dandruff SH and COND
NDC: 55319-320 | Form: SHAMPOO
Manufacturer: FAMILY DOLLAR SERVICES INC
Category: otc | Type: HUMAN OTC DRUG LABEL
Date: 20251208

ACTIVE INGREDIENTS: Pyrithione Zinc 10 mg/1 mL
INACTIVE INGREDIENTS: Water; SODIUM LAURETH-3 SULFATE; COCO MONOETHANOLAMIDE; Sodium Lauryl Sulfate; SODIUM XYLENESULFONATE; Sodium Chloride; MAGNESIUM SULFATE, UNSPECIFIED FORM; Glycol Distearate; Benzyl Alcohol; Cetyl Alcohol; CITRIC ACID MONOHYDRATE; GUAR HYDROXYPROPYLTRIMONIUM CHLORIDE; Dimethicone; Sodium Benzoate; POLYQUATERNIUM-10 (30000 MPA.S AT 2%); CAMPHOR (SYNTHETIC); MENTHOL, UNSPECIFIED FORM; Methylchloroisothiazolinone; Magnesium Carbonate Hydroxide; FD&C BLUE NO. 1; D&C RED NO. 33; Methylisothiazolinone

Equate™ Men's Bold Scent 2 in 1 Dandruff SH & COND
Anti-Dandruff

Drug Facts

Active ingredient

Pyrithione Zinc 1%

Purpose

Anti-dandruff

Use

helps prevent recurrence of flaking and itching associated with dandruff.

Warnings

For external use only

When using this product

- avoid contact with the eyes. If contact occurs, rinse eyes thoroughly with water

Stop use and ask a doctor if

- condition worsens or does not improve after regular use of this product as directed

Keep out of reach of children. If swallowed, get medical help or contact a Poison Control Center (1-800-222-1222) right away.

Directions

- shake well
- wet hair
- massage onto scalp
- rinse
- repeat if desired
- for best results use at least twice a week or as directed by a doctor
- for maximum dandruff control, use every time you shampoo

Other information

store at room temperature

Inactive ingredients

water, sodium laureth sulfate, cocamide MEA, sodium lauryl sulfate, sodium xylenesulfonate, sodium chloride, fragrance, magnesium sulfate, glycol distearate, benzyl alcohol, cetyl alcohol, citric acid, guar hydroxypropyltrimonium chloride, dimethicone, sodium benzoate, polyquaternium-10, ammonium laureth sulfate, camphor, menthol, methylchloroisothiazolinone, magnesium carbonate hydroxide, blue 1, red 33, methylisothiazolinone.

Questions or comments?

1-866-567-8600

DISTRIBUTED BY: Walmart Inc.,
Bentonville, AR 72716

PRINCIPAL DISPLAY PANEL - 369 mL Bottle Label

FAMILY WELLNESS

COMPARE TO ACTIVE

INGREDIENT IN HEAD

& SHOULDERS®*

MEN'S BOLD SCENT

DANDRUFF

SHAMPOO

2-in-1

PLUS CONDITIONER

pH balanced with

pyrithione zinc

- Advanced formula helps improve
  the health of hair and scalp

CEDARWOOD

& LIME SCENT

12.5 FL OZ (369 mL)

05-4943

FAMILY WELLNESS BOLD